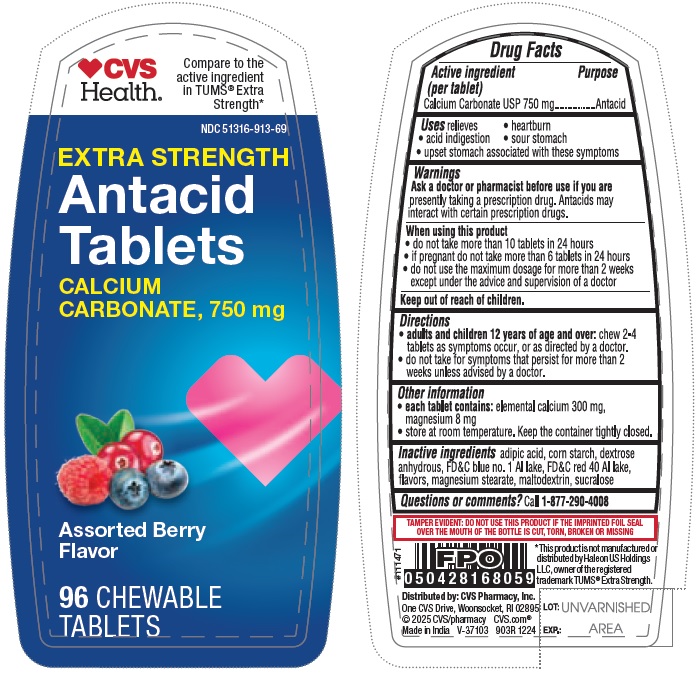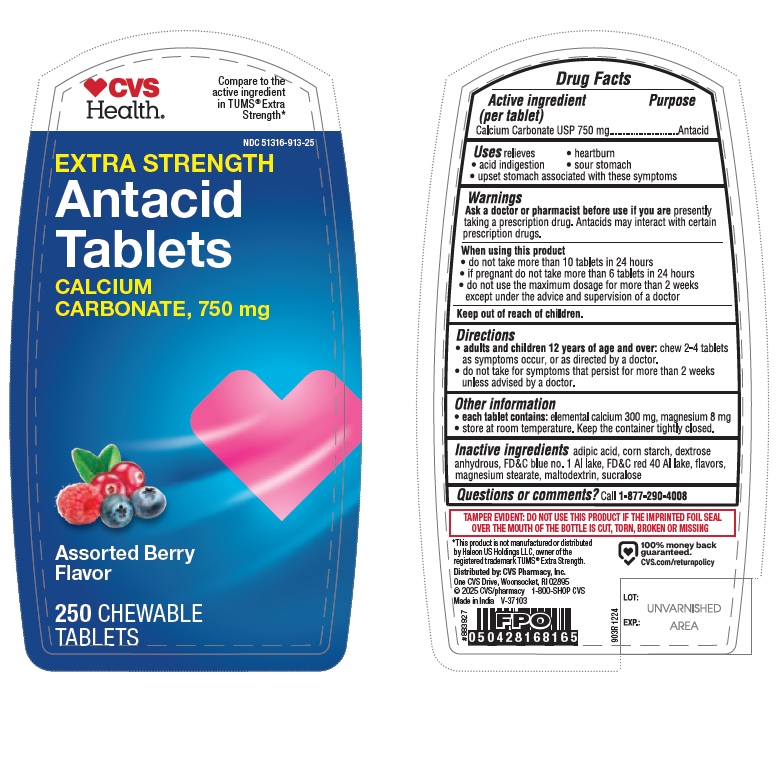 DRUG LABEL: Calcium Carbonate 750 mg
NDC: 51316-913 | Form: TABLET, CHEWABLE
Manufacturer: CVS Pharmacy.Inc.
Category: otc | Type: HUMAN OTC DRUG LABEL
Date: 20250409

ACTIVE INGREDIENTS: CALCIUM CARBONATE 750 mg/1 1
INACTIVE INGREDIENTS: MAGNESIUM STEARATE; ADIPIC ACID; FD&C BLUE NO. 1 ALUMINUM LAKE; MALTODEXTRIN; FD&C RED NO. 40 ALUMINUM LAKE; SUCRALOSE; STARCH, CORN; ANHYDROUS DEXTROSE

903R_CVS_51316-913_Calcium Carbonate 750 mg chewable tablets - Assorted Berries

Active ingredient (per tablet)

Calcium Carbonate USP 750 mg

Purpose

Antacid

INDICATIONS AND USAGE

Uses relieves

- heartburn
- acid indigestion
- sour stomach
- upset stomach associated with these symptoms

Warnings

Ask a doctor or pharmacist before use if you are presently taking a prescription drug. Antacids may interact with certain prescription drugs.

When using this product

- do not take more than 10 tablets in 24 hours
- if pregnant do not take more than 6 tablets in 24 hours
- do not use the maximum dosage for more than 2 weeks except under the advice and supervision of a doctor

Keep out of reach of children.

Directions

- adults and children 12 years of age and over: chew 2-4 tablets as symptoms occur, or as directed by a doctor.
- do not take for symptoms that persist for more than 2 weeks unless advised by a doctor.

Other information

- each tablet contains: elemental calcium 300 mg, magnesium 8 mg
- store at room temperature. Keep the container tightly closed.

INACTIVE INGREDIENT

Inactive ingredientsadipic acid, corn starch, dextrose anhydrous, FD&C blue no. 1 Al lake, FD&C red 40 Al lake, flavors, magnesium stearate, maltodextrin, sucralose

Questions or comments?Call 1-877-290-4008